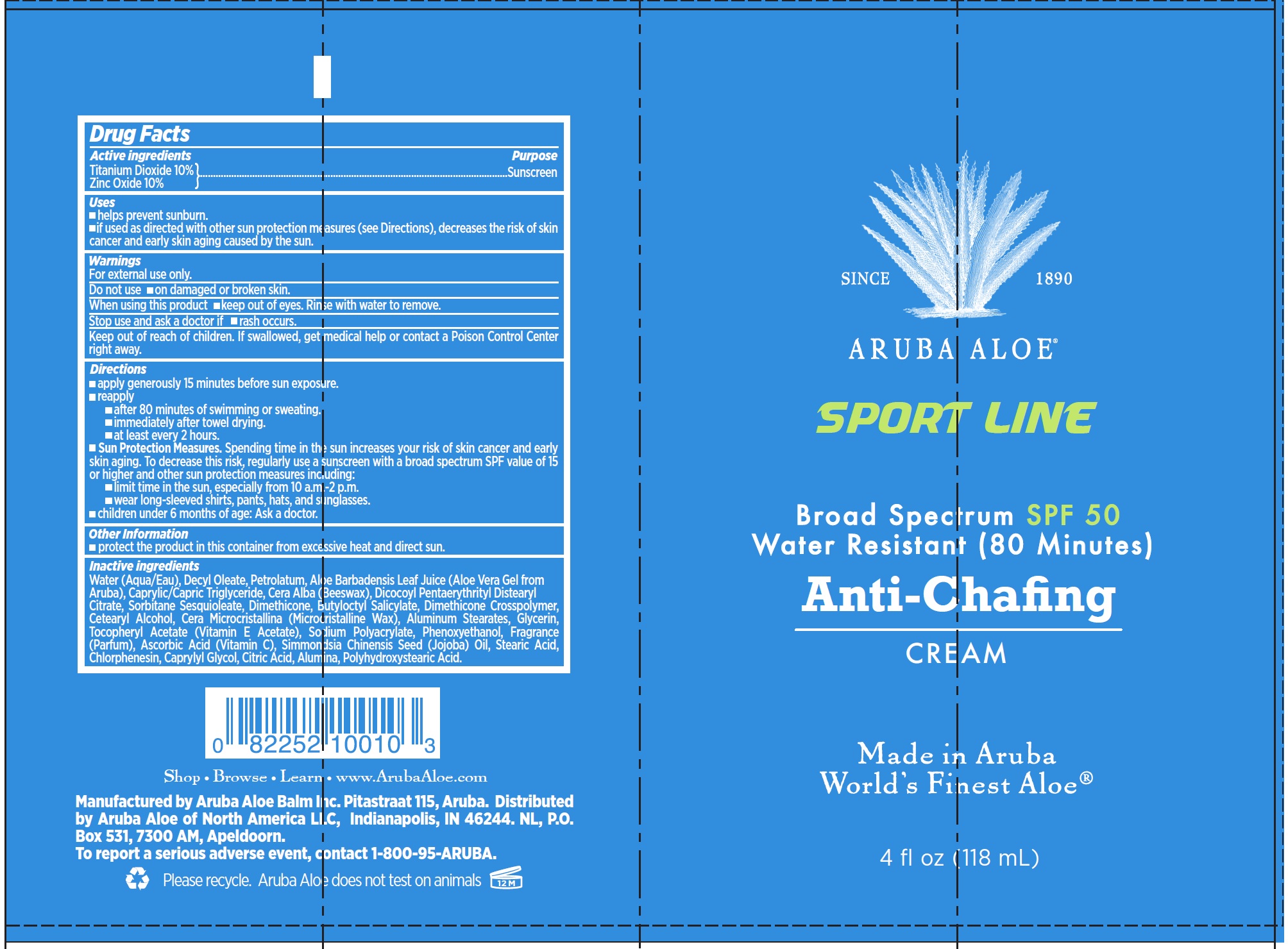 DRUG LABEL: Aruba Aloe Sport Line Broad Spectrum SPF 50 Anti Chafing
NDC: 53675-186 | Form: CREAM
Manufacturer: Aruba Aloe Balm NV
Category: otc | Type: HUMAN OTC DRUG LABEL
Date: 20231106

ACTIVE INGREDIENTS: TITANIUM DIOXIDE 100 mg/1 mL; ZINC OXIDE 100 mg/1 mL
INACTIVE INGREDIENTS: WATER; DECYL OLEATE; PETROLATUM; ALOE VERA LEAF; MEDIUM-CHAIN TRIGLYCERIDES; WHITE WAX; DICOCOYL PENTAERYTHRITYL DISTEARYL CITRATE; SORBITAN SESQUIOLEATE; DIMETHICONE; BUTYLOCTYL SALICYLATE; DIMETHICONE CROSSPOLYMER (450000 MPA.S AT 12% IN CYCLOPENTASILOXANE); CETOSTEARYL ALCOHOL; MICROCRYSTALLINE WAX; ALUMINUM STEARATES; GLYCERIN; .ALPHA.-TOCOPHEROL ACETATE; PHENOXYETHANOL; ASCORBIC ACID; JOJOBA OIL; STEARIC ACID; CHLORPHENESIN; CAPRYLYL GLYCOL; CITRIC ACID MONOHYDRATE; ALUMINUM OXIDE

Aruba Aloe Sport Line Broad Spectrum SPF 50 Anti-Chafing Cream

Active ingredients

Titanium Dioxide 10% Zinc Oxide 10%

Purpose

Sunscreen

Uses

- helps prevent sunburn.
- if used as directed with other sun protection measures (see Directions), decreases the risk of skin cancer and early skin aging caused by the sun.

Warnings

For external use only.

Do not use

- on damaged or broken skin.

When using this product

- keep out of eyes. Rinse with water to remove.

Stop use and ask a doctor if

- rash occurs.

Keep out of reach of children.

f swallowed, get medical help or contact a Poison Control Center right away.

Directions

- apply generously 15 minutes before sun exposure.
- reapply
- after 80 minutes of swimming or sweating.
- immediately after towel drying.
- at least every 2 hours.
- Spending time in the sun increases your risk of skin cancer and early skin aging. To decrease this risk, regularly use a sunscreen with a broad spectrum SPF value of 15 or higher and other sun protection measures including: Sun Protection Measures.
- limit time in the sun, especially from 10 a.m.-2 p.m.
- wear long-sleeved shirts, pants, hats, and sunglasses.
- children under 6 months of age: Ask a doctor.

Other Information

- protect the product in this container from excessive heat and direct sun.

Inactive ingredients

Water (Aqua/Eau), Decyl Oleate, Petrolatum, Aloe Barbadensis Leaf Juice (Aloe Vera Gel from Aruba), Caprylic/Capric Triglyceride, Cera Alba (Beeswax), Dicocoyl Pentaerythrityl Distearyl Citrate, Sorbitane Sesquioleate, Dimethicone, Butyloctyl Salicylate, Dimethicone Crosspolymer, Cetearyl Alcohol, Cera Microcristallina (Microcristalline Wax), Aluminum Stearates, Glycerin, Tocopheryl Acetate (Vitamin E Acetate), Sodium Polyacrylate, Phenoxyethanol, Fragrance (Parfum), Ascorbic Acid (Vitamin C), Simmondsia Chinensis Seed (Jojoba) Oil, Stearic Acid, Chlorphenesin, Caprylyl Glycol, Citric Acid, Alumina, Polyhydroxystearic Acid.